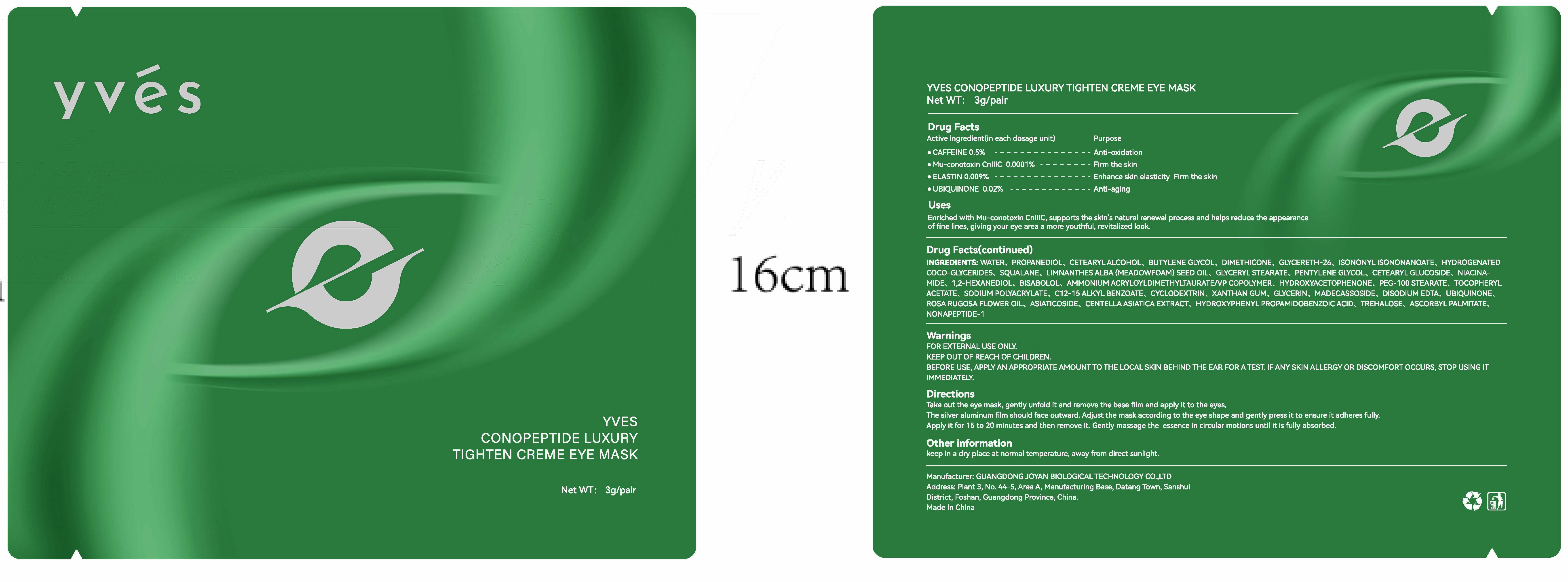 DRUG LABEL: YVES CONOPEPTIDE LUXURY TIGHTEN CREME EYE MASK
NDC: 85779-002 | Form: CREAM
Manufacturer: Guangdong Joyan Biological Technology Co.,Ltd
Category: otc | Type: HUMAN OTC DRUG LABEL
Date: 20250610

ACTIVE INGREDIENTS: .MU.-CONOTOXIN G IIIC 0.0001 g/100 g; ELASTIN 0.0009 g/100 g; UBIQUINONE 0.02 g/100 g; CAFFEINE 0.5 g/100 g
INACTIVE INGREDIENTS: WATER; PENTYLENE GLYCOL; 1,2-HEXANEDIOL

85779-002 YVES CONOPEPTIDE LUXURY TIGHTEN CREME EYE MASK

ACTIVE INGREDIENT

CAFFEINE 0.5%
Mu-conotoxin CnIIIC 0.0001%
ELASTIN 0.009%
UBIQUINONE 0.02%

PURPOSE

Anti-oxidation
Firm the skin
Enhance skin elasticity Firm the skin
Anti-aging

KEEP OUT OF REACH OF CHILDREN.

WARNINGS

FOR EXTERNAL USE ONLY.

INDICATIONS AND USAGE

Enriched with Mu-conotoxin Cnlllc, supports the skin's natural renewal process and helps reduce the appearance
of fine lines, giving your eye area a more youthful, revitalized look.

WHEN USING

BEFORE USE, APPLY AN APPROPRIATE AMOUNTTO THE LOCAL SKIN BEHIND THE EAR FOR A TEST IF ANYSKIN ALLERGY OR DISCOMFORT OCCURS, STOP USING IT
IMMEDIATELY.

Directions
Take out the eye mask, gently unfold it and remove the base film and apply it to the eyes.The silver aluminum film should face outward. Adjust the mask according to the eye shape and gently press it to ensure it adheres fully.Apply it for 15 to 20 minutes and then remove it. Gently massage the essence in circular motions until it is fully absorbed.

INACTIVE INGREDIENT

WATER
PENTYLENE GLYCOL
1,2-HEXANEDIOL